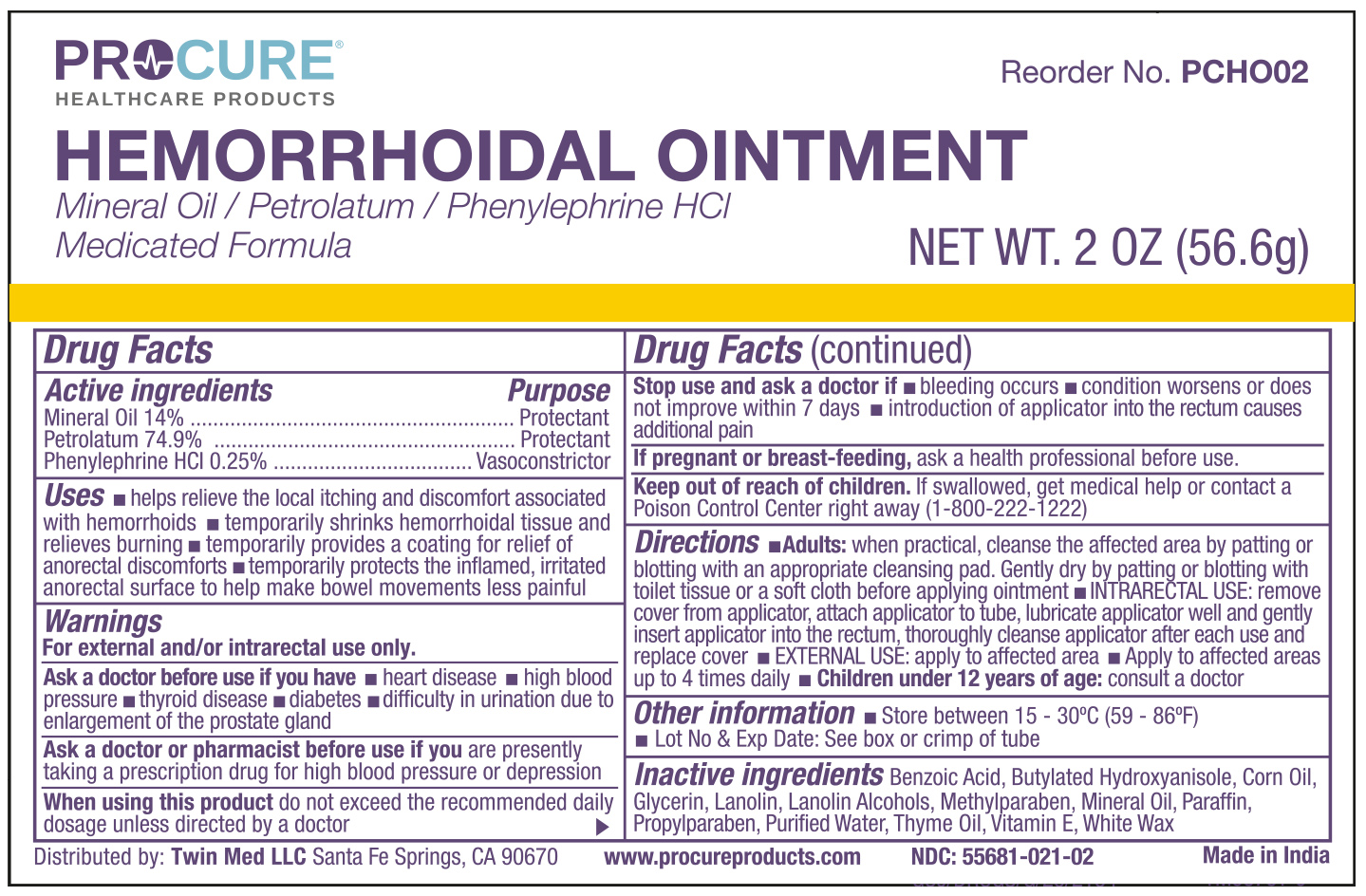 DRUG LABEL: ProCure Hemorrhoidal
NDC: 55681-021 | Form: OINTMENT
Manufacturer: Twin Med LLC
Category: otc | Type: HUMAN OTC DRUG LABEL
Date: 20250615

ACTIVE INGREDIENTS: PETROLATUM 74.9 g/100 g; PHENYLEPHRINE HYDROCHLORIDE 0.25 g/100 g; MINERAL OIL 14 g/100 g
INACTIVE INGREDIENTS: WATER; .ALPHA.-TOCOPHEROL ACETATE; PROPYLPARABEN; LANOLIN; PARAFFIN; WHITE WAX; BENZOIC ACID; LANOLIN ALCOHOLS; THYME OIL; BUTYLATED HYDROXYANISOLE; CORN OIL; METHYLPARABEN; GLYCERIN

Active Ingredients

Mineral Oil 14%

Petrolatum 74.9%

Phenylephrine HCl 0.25%

Purpose

Mineral Oil 14%......................Protectant

Petrolatum 74.9%...................Protectant

Phenylephrine HCl 0.25%......Vasoconstrictor

Uses

- helps relieve the local ithcing and discomfort associated with hemorrhoids
- temporarily shrinks hemorrhoidal tissue and relieves burning
- temporarity provides a coating for relief of anorectal discomforts
- temporarily protects the inflamed, irritated anorectal surface to help make bowel movements less painful

Warnings

for external and / or intrarectal use only.

Ask doctor before use if you have

- heart disease
- high blood pressure
- thyroid disease
- diabetes
- difficulty in urination due to enlargement of the prostate gland

Ask a doctor or pharmacist before use if you are presently taking a prescription drug for high blood pressure or depression

When using this product do not exceed the recommended daily dosage unless directed by a doctor

Stop use and ask a doctor if

- bleeding occurs
- condition worsens or does not improve within 7 days
- introduction of applicator into the rectum causes additional pain

If pregnant or breast-feeding, ask a health professional before use.

Keep out of reach of children. If swallowed, get medical help or contact a Poison Control Center right away (1-800-222-1222)

Directions

- Adults: when practical, cleanse the affected area by patting or blotting with an appropriate cleansing pad. Genrly dry by patting or blotting with toilet tissue or a soft cloth before applying ointment.
- INTERARECTAL USE: remove cover from applicator, attach applicator to tube, lubricate applicator well and gently insert applicator into the rectum, thoroughly cleanse applicator after each use and replace the cover.
- EXTERNAL USE: apply to affected area
- Apply to affected area up to 4 times daily
- Children under 12 yeras of age: consult a doctor.

Inactive ingredients

Inactive ingredients: Benzoic Acid, Betylated Hydroxyanisole, Corn Oil, Glycerin, Lanolin, Lanolin Alcohols, Methylparaben, Mineral Oil, Paraffin, Propylparaben, Purifed Water, Thyme Oil, Vitamin E, White Wax